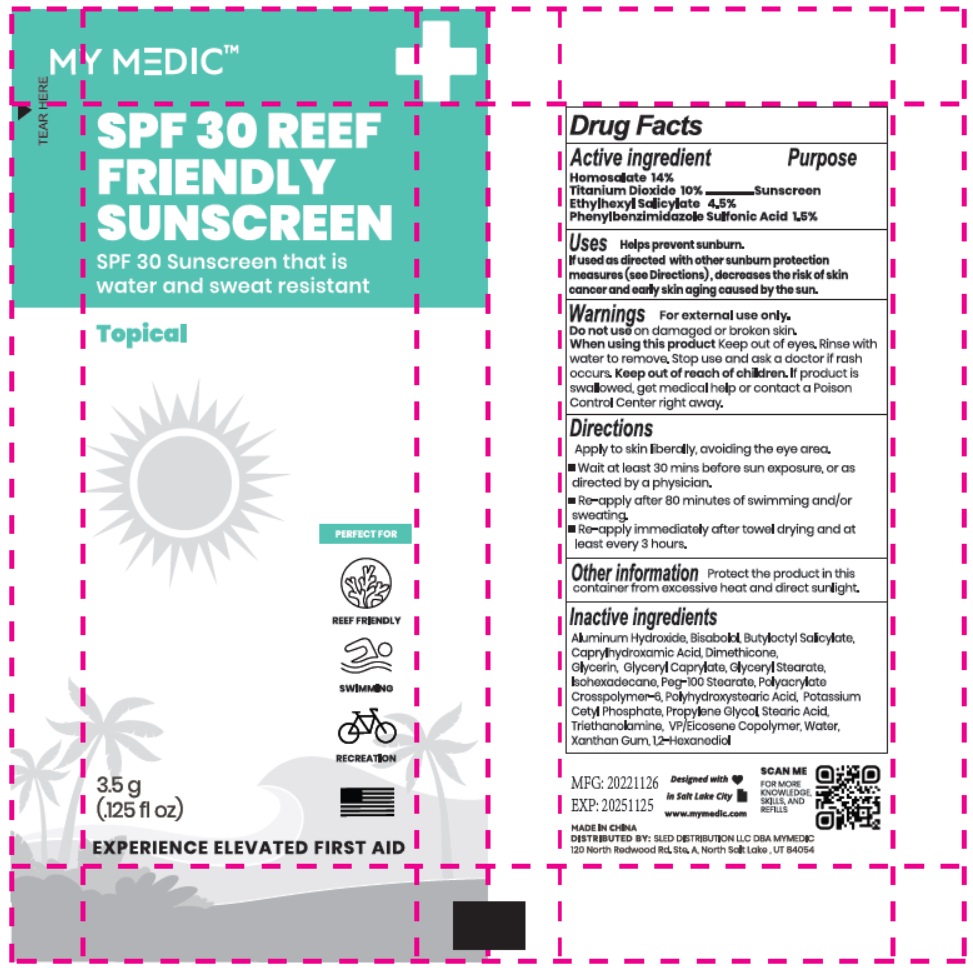 DRUG LABEL: MY MEDIC SPF 30 REEF FRIENDLY SUNSCREEN
NDC: 81417-009 | Form: CREAM
Manufacturer: Sled Distribution, LLC
Category: otc | Type: HUMAN OTC DRUG LABEL
Date: 20240115

ACTIVE INGREDIENTS: ENSULIZOLE 1.5 g/100 g; OCTISALATE 4.5 g/100 g; HOMOSALATE 14 g/100 g; TITANIUM DIOXIDE 10 g/100 g
INACTIVE INGREDIENTS: GLYCERYL CAPRYLATE; GLYCERYL MONOSTEARATE; BUTYLOCTYL SALICYLATE; GLYCERIN; DIMETHICONE; PEG-100 STEARATE; ALUMINUM HYDROXIDE; XANTHAN GUM; LEVOMENOL; POTASSIUM CETYL PHOSPHATE; CAPRYLHYDROXAMIC ACID; WATER; AMMONIUM ACRYLOYLDIMETHYLTAURATE, DIMETHYLACRYLAMIDE, LAURYL METHACRYLATE AND LAURETH-4 METHACRYLATE COPOLYMER, TRIMETHYLOLPROPANE TRIACRYLATE CROSSLINKED (45000 MPA.S); STEARIC ACID; ISOHEXADECANE; POLYHYDROXYSTEARIC ACID STEARATE; 1,2-HEXANEDIOL; VINYLPYRROLIDONE/EICOSENE COPOLYMER; TROLAMINE; PROPYLENE GLYCOL

81417-009 MY MEDIC SUNSCREEN SPF30

Active ingredient

Homosalate 14%

Titanium Dioxide 10%

Ethylhexyl Salicylate 4.5%

Phenylbenzimidazole Sulfonic Acid 1.5%

Purpose

Sunscreen

Uses

Helps prevent sunburn.

lf used as directed with other sunburn protection measures (see Directions), decreases the risk of skin cancer and early skin aging caused by the sun.

Warnings

- For external use only

- Do not use on damaged or broken skin

- When using this product keep out of eyes.

Rinse with water to remove.

- Stop use and ask a doctor if rash occurs

- Keep out of reach of children. If product is swallowed, get medical help or contact a Poison Control Center right away.

Directions

- Apply to skin liberally, avoiding the eye area.
- Wait at least 30 mins before sun exposure, or as directed by a physician.
- Re-apply after 80 mniutes of swimming and/or sweating.
- Re-apply immediately after towel drying and at least every 3 hours.

Inactive ingredients

Aluminum Hydroxide, Bisabolol, Butyloctyl Salicylate, Caprylhydroxamic Acid, Dimethicone, Glycerin, Glyceryl Caprylate, Glyceryl Stearate, lsohexadecane, Peg-100 Stearate, Polyacrylate Crosspolymer-6, Polyhydroxystearic Acid, Potassium Cetyl Phosphate, Propylene Glycol, Stearic Acid, Triethanolamine, VP Eicosene Copolymer, Water, Xanthan Gum, 1,2 Hexanediol